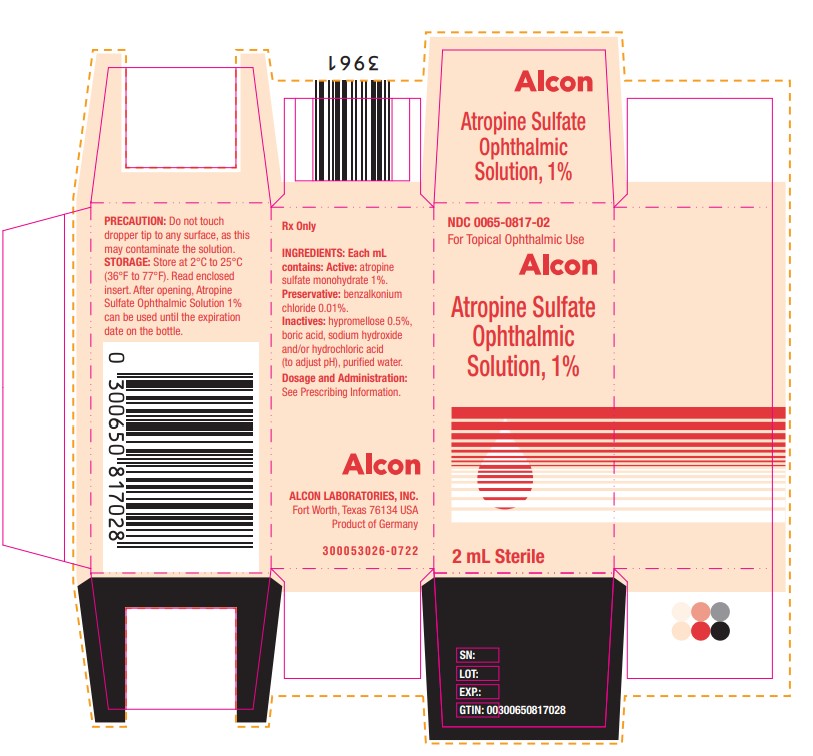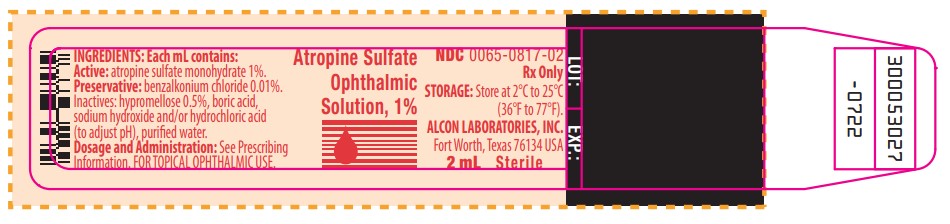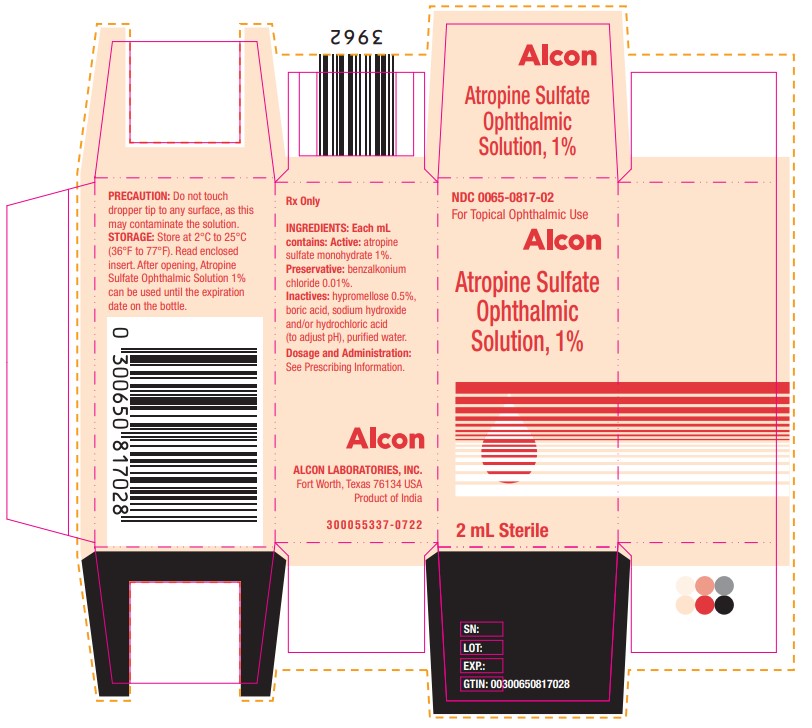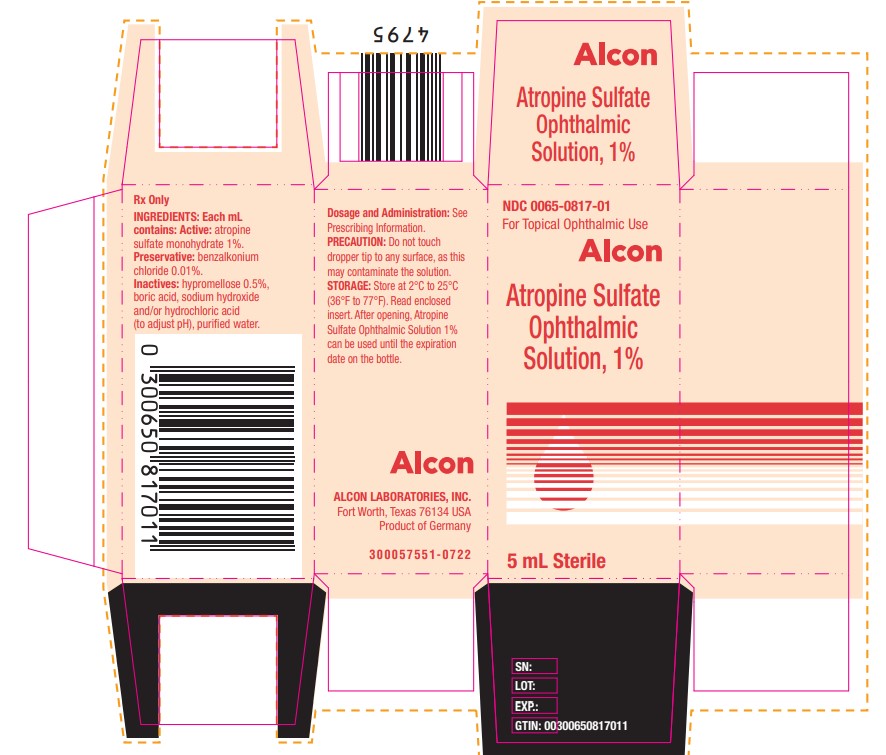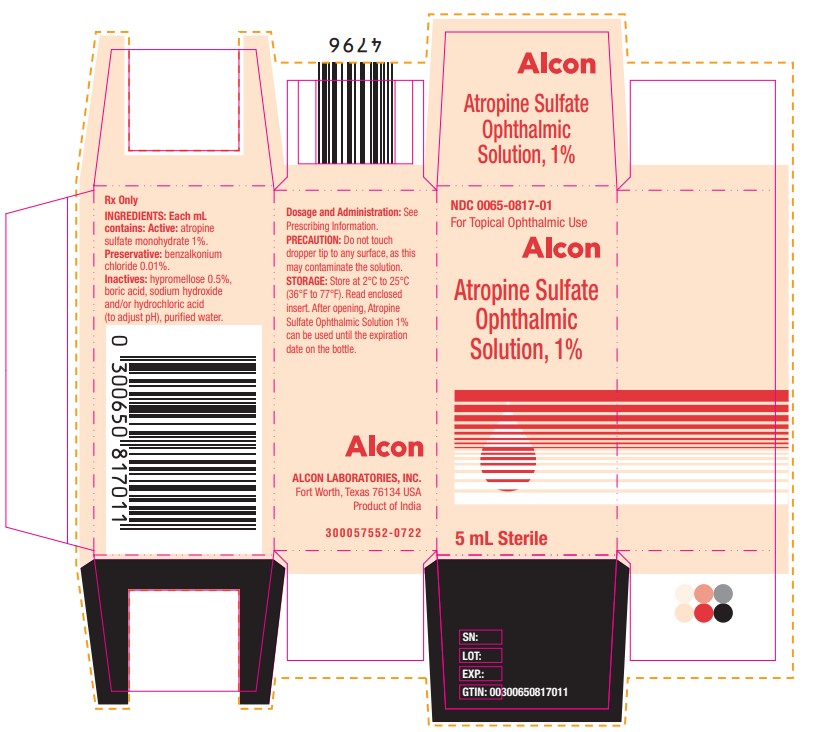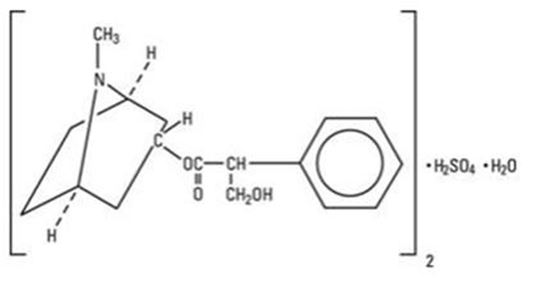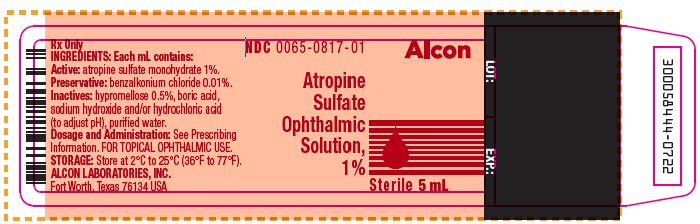 DRUG LABEL: atropine sulfate
NDC: 0065-0817 | Form: SOLUTION
Manufacturer: Alcon Laboratories, Inc.
Category: prescription | Type: HUMAN PRESCRIPTION DRUG LABEL
Date: 20250122

ACTIVE INGREDIENTS: Atropine Sulfate 10 mg/1 mL
INACTIVE INGREDIENTS: Benzalkonium Chloride; Hypromellose, Unspecified; Boric Acid; Sodium Hydroxide; Hydrochloric Acid; Water

HIGHLIGHTS OF PRESCRIBING INFORMATION

ATROPINE SULFATE - atropine sulfate solution
These highlights do not include all the information needed to use ATROPINE SULFATE OPHTHALMIC SOLUTION safely and effectively. See full prescribing information for ATROPINE SULFATE OPHTHALMIC SOLUTION.
ATROPINE SULFATE OPHTHALMIC SOLUTION, 1%, for topical ophthalmic use
Initial U.S. Approval 1960

1 INDICATIONS AND USAGE

Atropine Sulfate Ophthalmic Solution, 1% is a muscarinic antagonist indicated for:

- Mydriasis (1.1)
- Cycloplegia (1.2)
- Penalization of the healthy eye in the treatment of amblyopia (1.3)

2 DOSAGE AND ADMINISTRATION

- In individuals from three (3) months of age or greater 1 drop topically to the cul-de-sac of the conjunctiva, forty minutes prior to the intended maximal dilation time (2.1)
- In individuals 3 years of age or greater, doses may be repeated up to twice daily as needed. (2.2)

3 DOSAGE FORMS AND STRENGTHS

Ophthalmic solution: 1% atropine sulfate (10mg/mL) (3)

4 CONTRAINDICATIONS

- Hypersensitivity or allergic reaction to any ingredient in the formulation (4)

5 WARNINGS AND PRECAUTIONS

- Photophobia and blurred vision due to pupil unresponsiveness and cycloplegia may last up to 2 weeks. (5.1)
- Risk of blood pressure increase from systemic absorption (5.2)
- Increased adverse drug reaction susceptibility with certain central nervous system conditions (5.3)

6 ADVERSE REACTIONS

The most common adverse reactions that have been reported are eye pain and stinging on administration, blurred vision, photophobia, superficial keratitis, decreased lacrimation, drowsiness, increased heart rate and blood pressure. (6)

To report SUSPECTED ADVERSE REACTIONS, contact Alcon Laboratories, Inc., at 1-800-757-9195 or FDA at 1-800-FDA-1088 or www.fda.gov/medwatch.

7 DRUG INTERACTIONS

The use of atropine and monoamine oxidase inhibitors (MAOI) is generally not recommended because of the potential to precipitate hypertensive crisis. (7)

FULL PRESCRIBING INFORMATION

1 INDICATIONS AND USAGE

Atropine Sulfate Ophthalmic Solution, 1% is indicated for:

2 DOSAGE AND ADMINISTRATION

In individuals from three (3) months of age or greater, 1 drop topically to the cul-de-sac of the conjunctiva, forty minutes prior to the intended maximal dilation time.

In individuals 3 years of age or greater, doses may be repeated up to twice daily as needed.

3 DOSAGE FORMS AND STRENGTHS

Ophthalmic solution: 1% atropine sulfate (10mg/mL)

4 CONTRAINDICATIONS

Atropine sulfate ophthalmic solution should not be used in anyone who has demonstrated a previous hypersensitivity or known allergic reaction to any ingredient of the formulation because it may recur.

5 WARNINGS AND PRECAUTIONS

5.1 Photophobia and Blurred Vision

Photophobia and blurred vision due to pupil unresponsiveness and cycloplegia may last up to 2 weeks.

5.2 Elevation of Blood Pressure

Elevation in blood pressure from systemic absorption has been reported following conjunctival instillation of recommended doses of atropine sulfate ophthalmic solution, 1%.

5.3 Increased Adverse Drug Reaction Susceptibility with Certain Central Nervous System Conditions

Individuals with Down syndrome, spastic paralysis, or brain damage are particularly susceptible to central nervous system disturbances, cardiopulmonary, and gastrointestinal toxicity from systemic absorption of atropine.

6 ADVERSE REACTIONS

The following adverse reactions are described below and elsewhere in the labeling:

- Photophobia and Blurred Vision [see Warnings and Precautions (5.1)]
- Elevation in Blood Pressure [see Warnings and Precautions (5.2)]
- Increased Adverse Drug Reaction Susceptibility with Certain Central Nervous System Conditions [see Warnings and Precautions (5.3)]

The following adverse reactions have been identified following use of atropine sulfate ophthalmic solution. Because these reactions are reported voluntarily from a population of uncertain size, it is not always possible to reliably estimate their frequency or establish a causal relationship to drug exposure.

6.1 Ocular Adverse Reactions

Eye pain and stinging occurs upon instillation of atropine sulfate ophthalmic solution. Other commonly occurring adverse reactions include blurred vision, photophobia, superficial keratitis and decreased lacrimation. Allergic reactions such as papillary conjunctivitis, contact dermatitis, and eyelid edema may also occur less commonly.

6.2 Systemic Adverse Reactions

Systemic effects of atropine are related to its anti-muscarinic activity. Systemic adverse events reported include dryness of skin, mouth, and throat from decreased secretions from mucus membranes; drowsiness; restlessness, irritability or delirium from stimulation of the central nervous system; tachycardia; flushed skin of the face and neck.

7 DRUG INTERACTIONS

7.1 Monoamine Oxidase Inhibitors

The use of atropine and monoamine oxidase inhibitors (MAOI) is generally not recommended because of the potential to precipitate hypertensive crisis.

8 USE IN SPECIFIC POPULATIONS

8.1 Pregnancy

Risk Summary
There are no adequate and well-controlled studies with Atropine Sulfate Ophthalmic Solution, 1% administration in pregnant women to inform a drug-associated risk. Adequate animal development and reproduction studies have not been conducted with atropine sulfate. In humans, 1% atropine sulfate is systemically bioavailable following topical ocular administration [see Clinical Pharmacology (12.3)]. Atropine Sulfate Ophthalmic Solution, 1% should only be used during pregnancy if the potential benefit justifies the potential risk to the fetus.

8.2 Lactation

There is no information to inform risk regarding the presence of atropine in human milk following ocular administration of Atropine Sulfate Ophthalmic Solution, 1% to the mother. The effects on breastfed infants and the effects on milk production are also unknown. The developmental and health benefits of breastfeeding should be considered along with the mother’s clinical need for Atropine Sulfate Ophthalmic Solution, 1% and any potential adverse effects on the breastfed child from Atropine Sulfate Ophthalmic Solution, 1%.

8.4 Pediatric Use

Due to the potential for systemic absorption of atropine sulfate ophthalmic solution the use of Atropine Sulfate Ophthalmic Solution, 1% in children under the age of 3 months is not recommended and the use in children under 3 years of age should be limited to no more than one drop per eye per day. Safety and efficacy in children above the age of 3 months has been established in adequate and well controlled trials.

8.5 Geriatric Use

No overall differences in safety or effectiveness have been observed between elderly and adult patients.

10 OVERDOSAGE

In the event of accidental ingestion or toxic overdosage with atropine sulfate ophthalmic solution supportive care may include a short acting barbiturate or diazepam as needed to control marked excitement and convulsions. Large doses for sedation should be avoided because central depressant action may coincide with the depression occurring late in atropine poisoning. Central stimulants are not recommended.

Physostigmine, given by slow intravenous injection of 1 to 4 mg (0.5 to 1 mg in pediatric populations), rapidly abolishes delirium and coma caused by large doses of atropine. Since physostigmine is rapidly destroyed, the patient may again lapse into coma after one to two hours, and repeated doses may be required.

Artificial respiration with oxygen may be necessary. Cooling measures may be needed to help to reduce fever, especially in pediatric populations.

The fatal pediatric and adult doses of atropine are not known.

11 DESCRIPTION

Atropine Sulfate Ophthalmic Solution, 1% is a sterile topical ophthalmic solution. Each mL of Atropine Sulfate Ophthalmic Solution, 1% contains 10 mg of atropine sulfate monohydrate equivalent to 9.7 mg/mL of atropine sulfate or 8.3 mg of atropine. Atropine sulfate monohydrate is designated chemically as benzeneacetic acid, α-(hydroxymethyl)-,8-methyl-8-aza-bicyclo-[3.2.1]oct-3-yl ester, endo-(+)-, sulfate(2:1) (salt), monohydrate. Its molecular formula is (C17H23NO3)2 • H2SO4 • H2O and it is represented by the chemical structure:

Atropine sulfate monohydrate is colorless crystals or white crystalline powder and has a molecular weight of 694.83.

Atropine Sulfate Ophthalmic Solution, 1% has a pH of 3.5 to 6.0.

Active ingredient: atropine sulfate monohydrate 1%

Preservative: benzalkonium chloride 0.01%

Inactive ingredients: hypromellose, boric acid, sodium hydroxide and/or hydrochloric acid (to adjust pH), purified water.

12 CLINICAL PHARMACOLOGY

12.1 Mechanism of Action

Atropine acts as a competitive antagonist of the parasympathetic (and sympathetic) acetylcholine muscarinic receptors. Topical atropine on the eye induces mydriasis by inhibiting contraction of the circular pupillary sphincter muscle normally stimulated by acetylcholine. This inhibition allows the countering radial pupillary dilator muscle to contract which results in dilation of the pupil. Additionally, atropine induces cycloplegia by paralysis of the ciliary muscle which controls accommodation while viewing objects.

12.2 Pharmacodynamics

The onset of action after administration of Atropine Sulfate Ophthalmic Solution, 1% generally occurs in minutes with maximal effect seen in hours and the effect can last multiple days [see Clinical Studies (14)].

12.3 Pharmacokinetics

In a study of healthy subjects, after topical ocular administration of 30 μL of atropine sulfate ophthalmic solution, 1%, the mean (± SD) systemic bioavailability of l-hyoscyamine was reported to be approximately 64 ± 29% (range 19% to 95%) as compared to intravenous administration of atropine sulfate. The mean (± SD) time to maximum plasma concentration (Tmax) was approximately 28 ± 27 minutes (range 3 to 60 minutes), and the mean (±SD) peak plasma concentration (Cmax) of l-hyoscyamine was 288 ± 73 pg/mL. The mean (±SD) plasma half-life was reported to be approximately 2.5 ± 0.8 hours.

In a separate study of patients undergoing ocular surgery, after topical ocular administration of 40 μL of atropine sulfate ophthalmic solution, 1%, the mean (± SD) plasma Cmax of l-hyoscyamine was 860 ± 402 pg/mL.

13 NONCLINICAL TOXICOLOGY

13.1 Carcinogenesis, Mutagenesis, Impairment of Fertility

Atropine sulfate was negative in the Salmonella/microsome mutagenicity test. Studies to evaluate carcinogenicity and impairment of fertility have not been conducted.

14 CLINICAL STUDIES

Topical administration of Atropine Sulfate Ophthalmic Solution, 1% results in mydriasis and/or cycloplegia, with efficacy demonstrated in both adults and children. The maximum effect for mydriasis is achieved in about 30–40 minutes after administration, with recovery after approximately 7–10 days. The maximum effect for cycloplegia is achieved within 60–180 minutes after administration, with recovery after approximately 7–12 days.

16 HOW SUPPLIED/STORAGE AND HANDLING

Atropine Sulfate Ophthalmic Solution, 1% is supplied sterile in low-density polyethylene plastic DROP-TAINER® dispensers with low-density polyethylene tips and red polypropylene caps as follows:

- 2 mL filled in 4-mL bottles NDC 0065-0817-02
- 5 mL filled in 8-mL bottles NDC 0065-0817-01

Storage: Store Atropine Sulfate Ophthalmic Solution, 1% at 2°C to 25°C (36°F to 77°F). After opening, Atropine Sulfate Ophthalmic Solution 1% can be used until the expiration date on the bottle.

17 PATIENT COUNSELING INFORMATION

- Advise patients not to drive or engage in other hazardous activities while pupils are dilated.
- Advise patient that they may experience blurry vision and sensitivity to light and should protect their eyes in bright illumination during dilation. These effects may last up to a couple weeks.
- Advise patients that they may experience drowsiness.
- Advise patients not to touch the dispenser tip to any surface, as this may contaminate the solution.

Alcon
ALCON LABORATORIES, INC.
Fort Worth, Texas 76134 USA
© 2022 Alcon Inc.

PRINCIPAL DISPLAY PANEL

NDC 0065-0817-02
For Topical Ophthalmic Use
Alcon
Atropine Sulfate Ophthalmic Solution, 1%
2 mL Sterile
Rx Only
INGREDIENTS: Each mL contains: Active: atropine sulfate monohydrate 1%.
Preservative: benzalkonium chloride 0.01%.
Inactives: hypromellose 0.5%, boric acid, sodium hydroxide and/or hydrochloric acid (to adjust pH), purified water.
Dosage and Administration: See Prescribing Information.
PRECAUTION: Do not touch dropper tip to any surface, as this may contaminate the solution.
STORAGE: Store at 2°C to 25°C (36°F to 77°F). Read enclosed insert. After opening, Atropine Sulfate Ophthalmic Solution 1% can be used until the expiration date on the bottle.
Alcon
ALCON LABORATORIES, INC.
Fort Worth, Texas 76134 USA
Product of India
300055337-0722

PRINCIPAL DISPLAY PANEL

NDC 0065-0817-02
For Topical Ophthalmic Use
Alcon
Atropine Sulfate Ophthalmic Solution, 1%
2 mL Sterile
Rx Only
INGREDIENTS: Each mL contains: Active: atropine sulfate monohydrate 1%.
Preservative: benzalkonium chloride 0.01%.
Inactives: hypromellose 0.5%, boric acid, sodium hydroxide and/or hydrochloric acid (to adjust pH), purified water.
Dosage and Administration: See Prescribing Information.
PRECAUTION: Do not touch dropper tip to any surface, as this may contaminate the solution.
STORAGE: Store at 2°C to 25°C (36°F to 77°F). Read enclosed insert. After opening, Atropine Sulfate Ophthalmic Solution 1% can be used until the expiration date on the bottle.
Alcon
ALCON LABORATORIES, INC.
Fort Worth, Texas 76134 USA
Product of Germany
300053026-0722

PRINCIPAL DISPLAY PANEL

Atropine Sulfate Ophthalmic Solution, 1%
NDC 0065-0817-02
Rx Only
STORAGE: Store at 2°C to 25°C (36°F to 77°F).
ALCON LABORATORIES, INC.
Fort Worth, Texas 76134 USA
2 mL Sterile
INGREDIENTS: Each mL contains: Active: atropine sulfate monohydrate 1%.
Preservative: benzalkonium chloride 0.01%.
Inactives: hypromellose 0.5%, boric acid, sodium hydroxide and/or hydrochloric acid (to adjust pH), purified water.
Dosage and Administration: See Prescribing information. FOR TOPICAL OPHTHALMIC USE

PRINCIPAL DISPLAY PANEL

NDC 0065-0817-01
For Topical Ophthalmic Use
Alcon
Atropine Sulfate Ophthalmic Solution, 1%
5 mL Sterile
Dosage and Administration: See Prescribing Information.
PRECAUTION: Do not touch dropper tip to any surface, as this may contaminate the solution.
STORAGE: Store at 2°C to 25°C (36°F to 77°F). Read enclosed insert. After opening, Atropine Sulfate Ophthalmic Solution 1% can be used until the expiration date on the bottle.
Rx Only
INGREDIENTS: Each mL contains: Active: atropine sulfate monohydrate 1%.
Preservative: benzalkonium chloride 0.01%.
Inactives: hypromellose 0.5%, boric acid, sodium hydroxide and/or hydrochloric acid (to adjust pH), purified water.
Alcon
ALCON LABORATORIES, INC.
Fort Worth, Texas 76134 USA
Product of Germany
300057551-0722

PRINCIPAL DISPLAY PANEL

NDC 0065-0817-01
For Topical Ophthalmic Use
Alcon
Atropine Sulfate Ophthalmic Solution, 1%
5 mL Sterile
Dosage and Administration: See Prescribing Information.
PRECAUTION: Do not touch dropper tip to any surface, as this may contaminate the solution.
STORAGE: Store at 2°C to 25°C (36°F to 77°F). Read enclosed insert. After opening, Atropine Sulfate Ophthalmic Solution 1% can be used until the expiration date on the bottle.
Rx Only
INGREDIENTS: Each mL contains: Active: atropine sulfate monohydrate 1%.
Preservative: benzalkonium chloride 0.01%.
Inactives: hypromellose 0.5%, boric acid, sodium hydroxide and/or hydrochloric acid (to adjust pH), purified water.
Alcon
ALCON LABORATORIES, INC.
Fort Worth, Texas 76134 USA
Product of India
300057552-0722

PRINCIPAL DISPLAY PANEL

Atropine Sulfate Ophthalmic Solution, 1%
NDC 0065-0817-01
Sterile 5 mL
Rx Only
INGREDIENTS: Each mL contains: Active: atropine sulfate monohydrate 1%.
Preservative: benzalkonium chloride 0.01%.
Inactives: hypromellose 0.5%, boric acid, sodium hydroxide and/or hydrochloric acid (to adjust pH), purified water.
Dosage and Administration: See Prescribing information. FOR TOPICAL OPHTHALMIC USE
STORAGE: Store at 2°C to 25°C (36°F to 77°F).
ALCON LABORATORIES, INC.
Fort Worth, Texas 76134 USA
300058444-0722